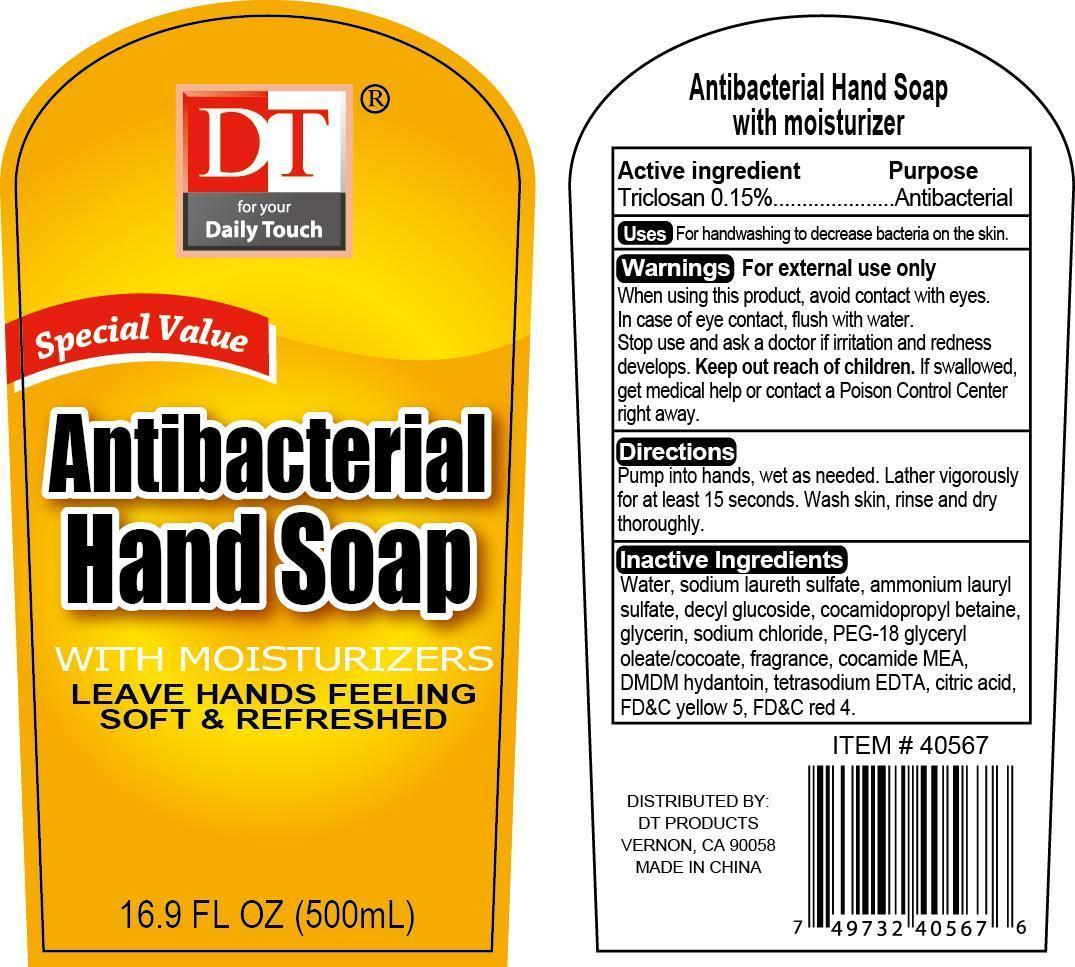 DRUG LABEL: Antibacterial Hand Cleanse
NDC: 58503-083 | Form: SOAP
Manufacturer: China Ningbo Shangge Cosmetic Technology Corp.
Category: otc | Type: HUMAN OTC DRUG LABEL
Date: 20150714

ACTIVE INGREDIENTS: TRICLOSAN 0.15 g/100 g
INACTIVE INGREDIENTS: WATER; SODIUM LAURETH SULFATE; AMMONIUM LAURYL SULFATE; DECYL GLUCOSIDE; COCAMIDOPROPYL BETAINE; GLYCERIN; SODIUM CHLORIDE; PEG-18 GLYCERYL OLEATE/COCOATE; COCO MONOETHANOLAMIDE; DMDM HYDANTOIN; EDETATE SODIUM; CITRIC ACID MONOHYDRATE; FD&C YELLOW NO. 5; FD&C RED NO. 4

Active Ingredient Purpose

Triclosan 0.15% ................. Antibacterial

PURPOSE

Uses For handwashing to decrease bacteria on the skin.

Keep out of reach of children. If swallowed, get medical help or contact a Poison Control Center right away.

INDICATIONS AND USAGE

DT for your DailyTouch

Special Value

Antibacterial Hand Soap

with moisturizers

leave hands feeling soft & refreshed

Directions

Pump into hands, wet as needed. Lather vigorously for at least 15 seconds. Wash skin, rinse and dry thoroughly.

Warnings For external use only

When using this product, avoid contact with eyes. In case of eye contact, flush with water. Stop use and ask a dctor if irritation and redness develops.

Inactive Ingredients

water, sodium laureth sulfate, ammonium lauryl sulfate, decyl glucoside, cocamidopropyl betaine, glycerin, sodium chloride, PEG-18 glyceryl oleate/cocoate, fragrance, cocamide MEA, DMDM hydantoin, tetrasodium EDTA, citric acid, FD&C yellow 5, FD&C red 4.